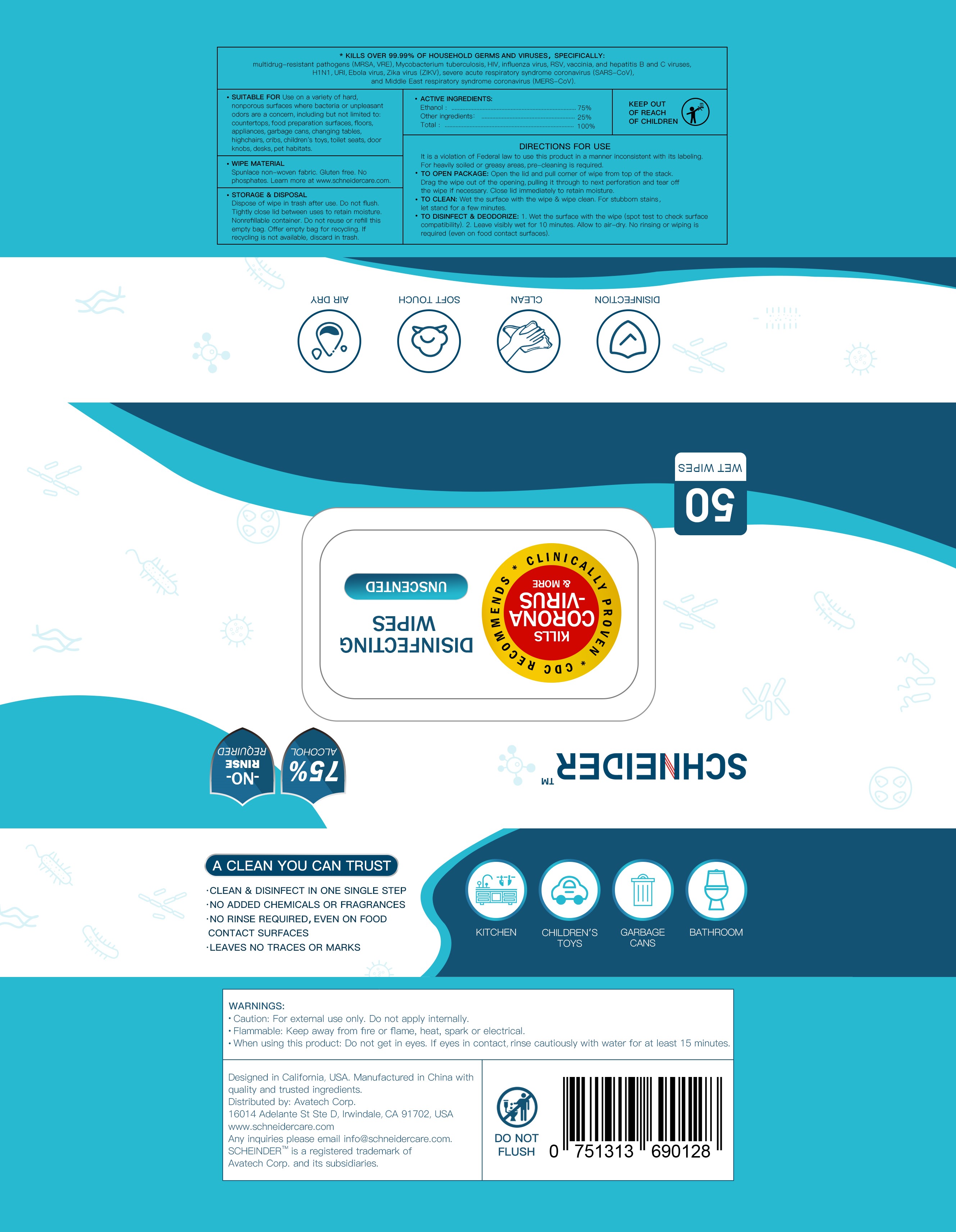 DRUG LABEL: Alcohol Wipes
NDC: 78450-001 | Form: CLOTH
Manufacturer: Avatech Corp.
Category: otc | Type: HUMAN OTC DRUG LABEL
Date: 20200628

ACTIVE INGREDIENTS: ALCOHOL 3.5 mL/1 1
INACTIVE INGREDIENTS: WATER

78450-001

Active Ingredient(s)

Alcohol 75% v/v. Purpose: Antiseptic

Inactive ingredients

Water

Purpose

SUITABLE FOR : Use on a varlety of hard, nonporous surfaces where bacteria or unpleasant odors are a concern, including but not limited to: countertops, food preparation surfaces, floors, appliances, garbage cans, changing tables, appliances, garbage cans,changing tables, highchairs,cribs,children's toys, toilet seats,door knobs,desks,pet habitats.

WHEN USING

This product is used to wipe hands, faces, skins, etc. It can also be used to clean many kinds of places.

Do not use

on children less than 2 months of age
on open skin wounds

STOP USE

if irritation or rash occurs.

These may be signs of a serious condition.

Keep out of reach of children.

Use

DIRECTIONS FOR USE:

It is a violation of Federal law to use this product in a manner inconsistent with its labeling. For heavily soiled or greasy areas, pre-cleaning is required.

TO OPEN PACKAGE:

Open the lid and pull corner of wipe from top of the stack. Drag the wipe out of the opening, pulling it through to next perforation and tear off the wipe if necessary. Close lid immediately to retain moistrue.

TO CLEAN:

Wet the surface with the wipe & wipe clean. For stubbom stains, let stand for a few minutes.

TO DISINFECT & DEODORIZE:

1. Wet the surface with the wipe (spot test to check surface compatibility).

2 . Leave visibly wet for 10 minutes. Allow to air-dry. No rinsing or wiping is required (even on food contact surfaces).

WIPE MATERIAL:

Spunlace non-woven fabric Gluten free. No phosphates. Learn more at www.schneidercare.com

Directions

Use it as needed, after following the usage instructions.

For external use only.

Warnings

Do not apply this product to red and swollen skin, wound or any part sensitive to it.

Keep this product out of children’s reach in case they might eat it.
Alcohol is violatile, please use it as soon as possible after opening, store it in a cool and dry place, avoid direct sunlight and open fire, and avoid contact with eyes and damaged skin.

Other information

- Store between 15-30C (59-86F)
- Avoid freezing and excessive heat above 40C (104F)
- Dispose of wipe in trash after use. Do not flush. Tightly close lid between uses to retain moisture. Non refillable container. Do not reuse or refill this empty bag. Offer empty bag for recycling. If recycling is not available, discard in trash.

Package Label - Principal Display Panel

50 CLOTH IN 1 BAG NDC:78450-001-01

1 CLOTH IN 1 BAG NDC:78450-001-02

10 CLOTH IN 1 BAG NDC:78450-001-03

80 CLOTH IN 1 BAG NDC:78450-001-04